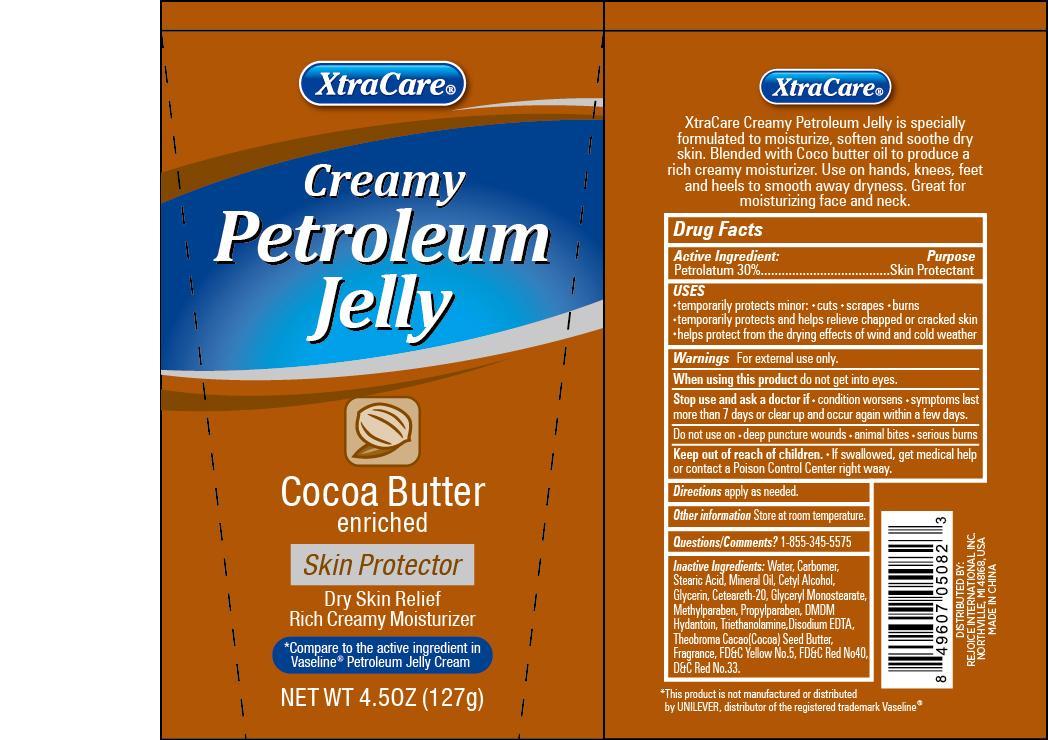 DRUG LABEL: XtraCare Creamy Petroleum Jelly
NDC: 57337-060 | Form: JELLY
Manufacturer: Rejoice International
Category: otc | Type: HUMAN OTC DRUG LABEL
Date: 20250211

ACTIVE INGREDIENTS: PETROLATUM 38 g/127 g
INACTIVE INGREDIENTS: WATER; CARBOMER COPOLYMER TYPE A (ALLYL PENTAERYTHRITOL CROSSLINKED); STEARIC ACID; MINERAL OIL; CETYL ALCOHOL; GLYCERIN; POLYOXYL 20 CETOSTEARYL ETHER; GLYCERYL MONOSTEARATE; METHYLPARABEN; PROPYLPARABEN; DMDM HYDANTOIN; TROLAMINE; EDETATE SODIUM; COCOA BUTTER; FD&C YELLOW NO. 5; FD&C RED NO. 40; D&C RED NO. 33

XtraCare Creamy Petroleum Jelly

Active Ingredient: Purpose

Petrolatum 30% ................................ Skin Protectant

Uses

- temporarily protects minor: cuts, scrapes, burns
- temporarily protects and helps relieve chapped or cracked skin
- helps protect from the drying effects of wind and cold weather

Keep out of reach of children. If swallowed, get medical help or contact a Poison Control Center right away.

INDICATIONS AND USAGE

XtraCare® Creamy Petroleum Jelly

Cocoa Butter enriched

Skin Protector

Dry Skin Relief

Rich Creamy Moisturiser

*Compare to the active ingredient in Vaseline® Petroleum Jelly Cream

Net Wt 4.5oz (127g)

Xtracare®

XtraCare Creamy Petroleum Jelly is specially formulated to moisturize, soften and soothe dry skin. Blended with Coco butter oil to product a rich creamy moisturizer. Use on hands, knees, feet and heels to smooth away dryness. Great for moisturizing face and neck.

Warnings

for external use only.

When using this product do not get into eyes.

Stop use and ask a doctor if

- condition worsens
- symptoms last more than 7 days or clear up and occur again within a few days

Do not use on

- deep puncture wounds
- animal bites
- serious burns

DOSAGE AND ADMINISTRATION

Directions apply as needed.

Inactive Ingredients:

water, carbomer, stearic acid, mineral oil, cetyl alcohol, glycerin, ceteareth-20, glyceryl monostearate, methylparaben, propylparaben, DMDM hydantoin, triethanolamine, disodium EDTA, theobroma cacao (cocoa) seed butter, fragrance, FD&C yellow no.5, FD&C red no.40, D&C red no.33.

Other informationstore at room temperature.

Questions/Comments? 1-855-345-5575

*this product is nor manufactured or distributed by UNILEVER, distributor of the registered trademark Vaseline®.

DISTRIBUTED BY

REJOICE INTERNATIONAL INC

NORTHVILLE, MI 48168 USA

MADE IN CHINA